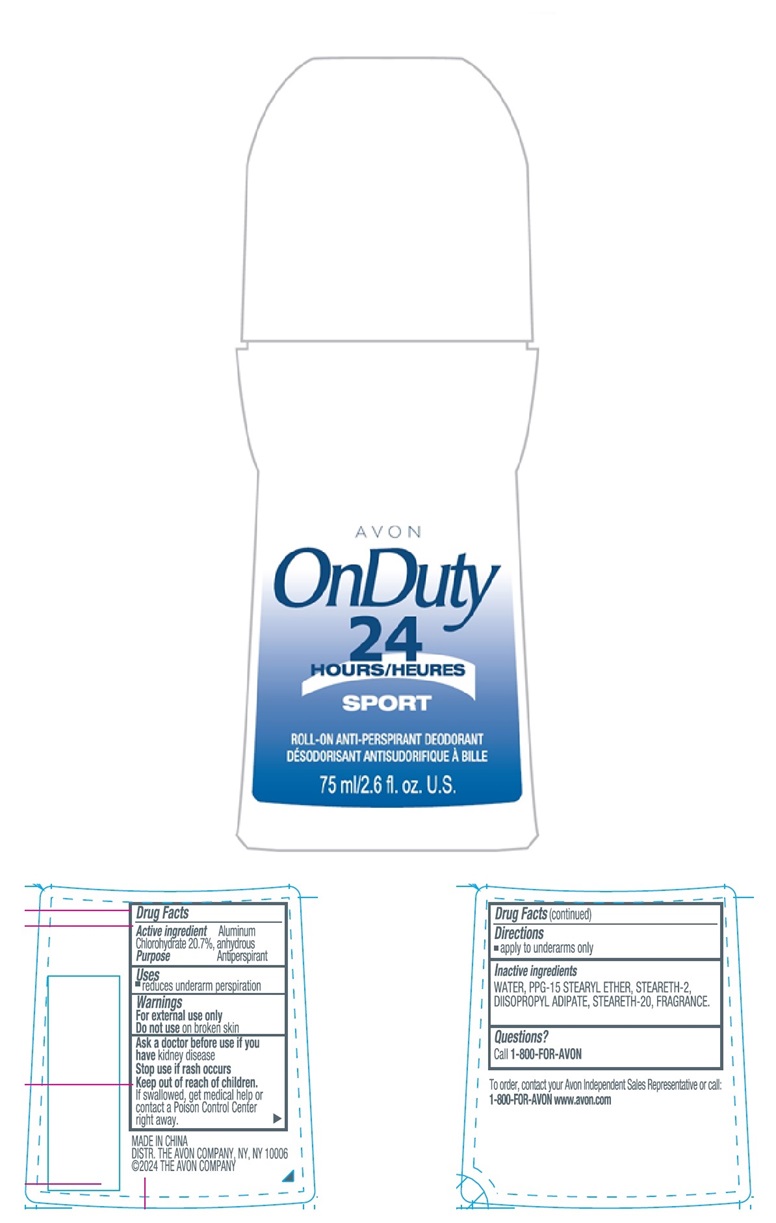 DRUG LABEL: AVON OnDuty 24 Hours Sport
NDC: 10096-1275 | Form: STICK
Manufacturer: The Avon Company
Category: otc | Type: HUMAN OTC DRUG LABEL
Date: 20240524

ACTIVE INGREDIENTS: ALUMINUM CHLOROHYDRATE 207 mg/1 mL
INACTIVE INGREDIENTS: STEARETH-2; WATER; DIISOPROPYL ADIPATE; PPG-15 STEARYL ETHER; STEARETH-20

AVON OnDuty 24 Hours Sport Roll-On Anti-Perspirant Deodorant 75ml

Active ingredient

Aluminum Chlorohydrate 20.7% anhydrous

Purpose

Antiperspirant

Uses

- reduces underarm perspiration

Warnings

For external use only

Do not use on broken skin

Ask a doctor before use if you have kidney disease

Stop use if rash occurs

Keep out of reach of children.
If swallowed, get medical help or contact a Poison Control Center right away.

Directions

- apply to underarms only

Inactive ingredients

WATER, PPG-15 STEARYL ETHER, STEARETH-2, DIISOPROPYL ADIPATE, STEARETH-20, FRANGRANCE

Questions?

Call 1-800-FOR-AVON

To order, contact your Avon Independent Sales Representative or call:
1-800-FOR-AVON www.avon.com

MADE IN CHINA
DIST. THE AVON COMPANY, NY, NY 10006
©2024 THE AVON COMPANY C2267486

Principal Display Panel

AVON
OnDuty
24
HOURS
SPORT
ROLL-ON ANTI-PERSPIRANT DEODORANT
75 ml/2.6 fl.oz. U.S.